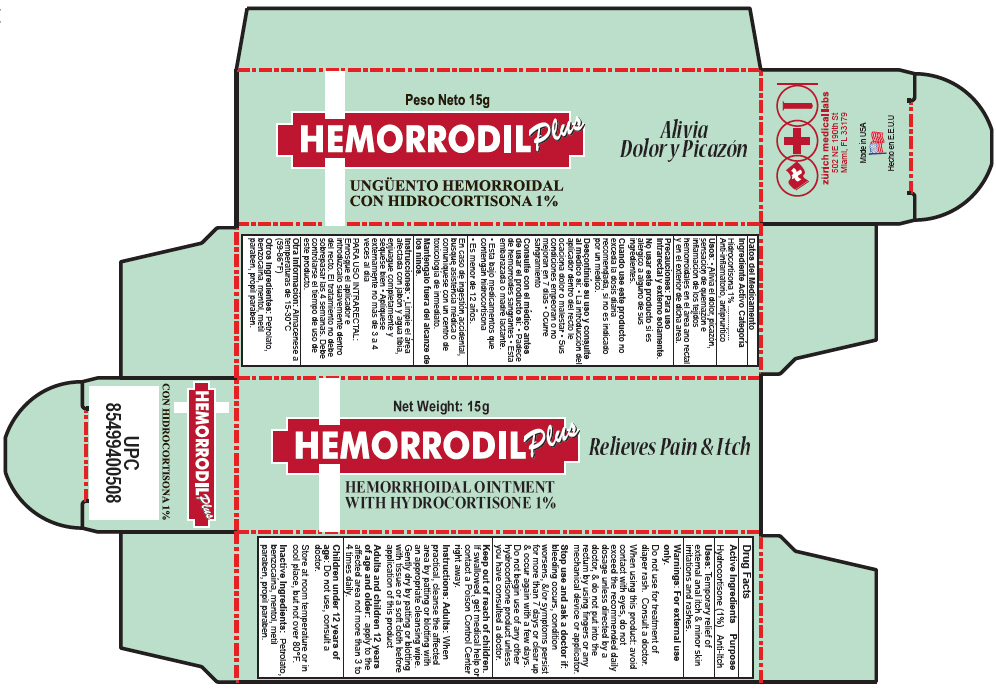 DRUG LABEL: Hemorrodil Unguento Plus
NDC: 61357-132 | Form: OINTMENT
Manufacturer: ZURICH MEDICAL LABS, LLC
Category: otc | Type: HUMAN OTC DRUG LABEL
Date: 20140311

ACTIVE INGREDIENTS: Hydrocortisone 10 mg/1 g
INACTIVE INGREDIENTS: BENZOCAINE; PETROLATUM; MENTHOL; METHYLPARABEN; PROPYLPARABEN

Hemorrodil Unguento Plus

Drug Facts

Active Ingredients

Hydrocortisone (1%)

Purpose

Anti-Itch

Uses

Temporary relief of external anal itch & minor skin irritations and rashes.

Warnings

For external use only.

Do not use for treatment of diaper rash. Consult a doctor.

When using this product: avoid contact with eyes, do not exceed the recommended daily dosage unless directed by a doctor, & do not put into the rectum by using fingers or any mechanical device or applicator.

Stop use and ask a doctor if: bleeding occurs, condition worsens, &/or symptoms persist for more than 7 days or clear up & occur again with a few days. Do not begin use of any other hydrocortisone product unless you have consulted a doctor.

Keep out of reach of children. If swallowed, get medical help or contact a Poison Control Center right away.

Instructions

Adults

When practical, cleanse the affected area by patting or blotting with an appropriate cleansing wipe. Gently dry by patting or blotting with tissue or a soft cloth before application of this product

Adults and children 12 years of age and older: apply to the affected area not more than 3 to 4 times daily.

Children under 12 years of age

Do not use, consult a doctor.

STORAGE AND HANDLING

Store at room temperature or in cool place, but not over 80°F.

Inactive Ingredients

Petrolato, benzocaína, mentol, metil paraben, propil paraben.

PRINCIPAL DISPLAY PANEL - 15 g Tube Carton

Net Weight: 15g

HEMORRODIL Plus
Relieves Pain & Itch

HEMORRHOIDAL OINTMENT
WITH HYDROCORTISONE 1%